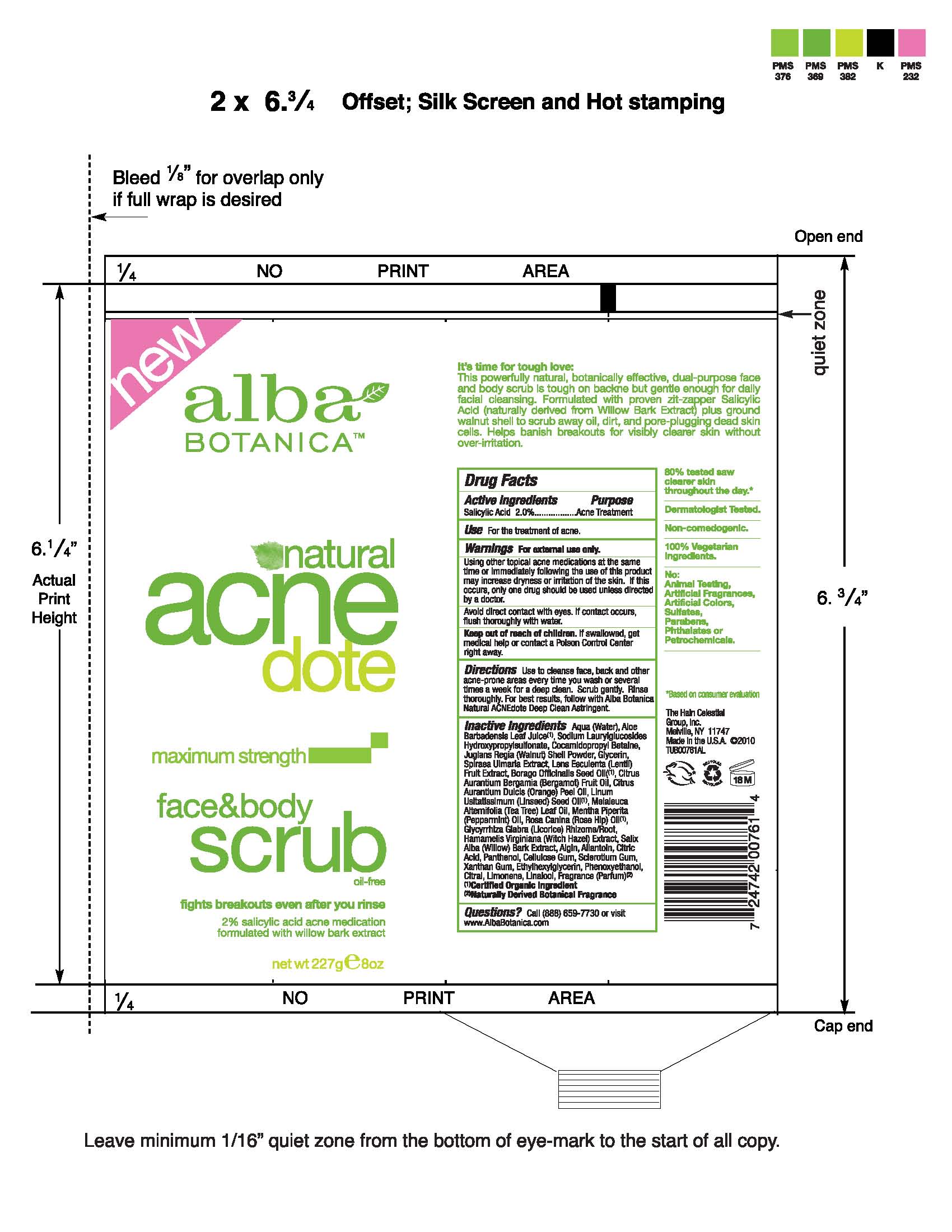 DRUG LABEL: Alba Natural Acnedote Face Body Scrub
NDC: 61995-2761 | Form: CREAM
Manufacturer: The Hain Celestial Group, Inc.
Category: otc | Type: HUMAN OTC DRUG LABEL
Date: 20100719

ACTIVE INGREDIENTS: Salicylic Acid 2.0 g/100 g

Drug Facts

ACTIVE INGREDIENTS

Salicylic Acid 2.0%

USE

- For the treatment of acne
- Use to cleanse face back and other acne-prone areas every time you wash or several time a week for a deep clean. Scrub gently. Rinse thoroughly
- For the best results, follow with Alba Botanica Natural ACNEdote Deep Clean Astringent

WARNINGS

For external use only. Using other topical acne medications at the same time or immediately following the use of this product may increase dryness or irritation of the skin. If this occurs,only one drug should be used unless directed by a doctor.

Avoid direct contact with eyes. If contact occurs, flush thoroughly with water.

Keep out of reach of children. If swallowed, get medical help or contact a Poison Control Center right away.